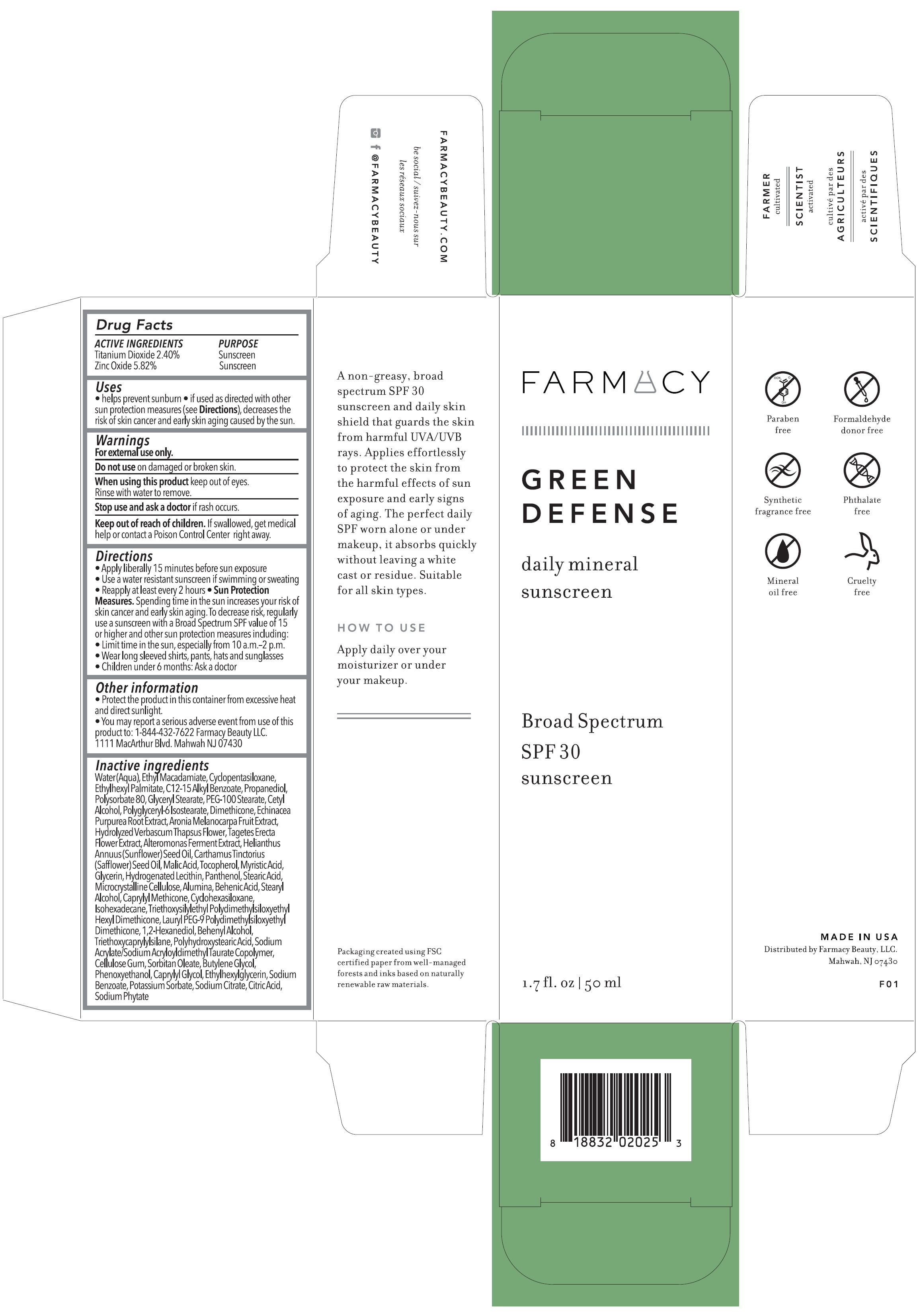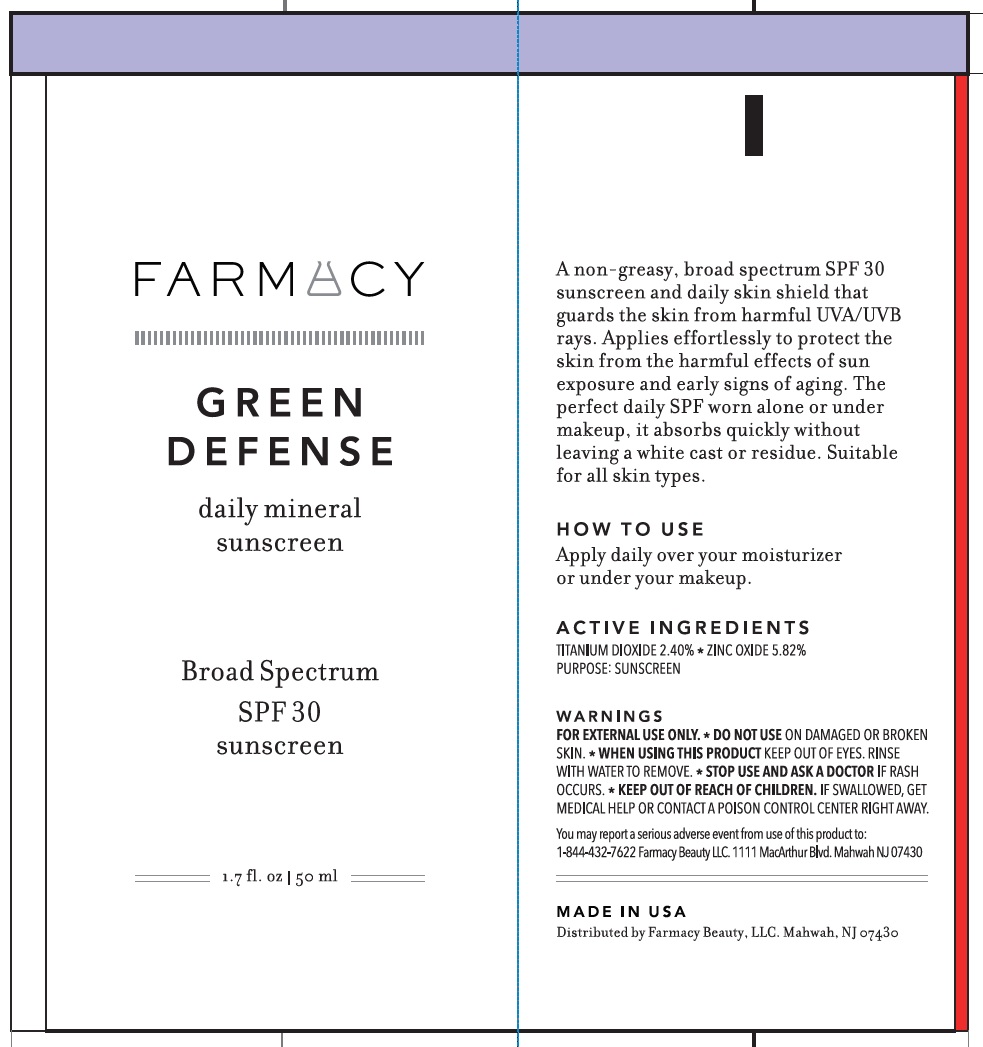 DRUG LABEL: Green Defense Broad Spectrum SPF 30
NDC: 72830-261 | Form: LOTION
Manufacturer: Farmacy Beauty LLC
Category: otc | Type: HUMAN OTC DRUG LABEL
Date: 20250102

ACTIVE INGREDIENTS: TITANIUM DIOXIDE 24 mg/1 mL; ZINC OXIDE 58.2 mg/1 mL
INACTIVE INGREDIENTS: WATER; ETHYL MACADAMIATE; CYCLOMETHICONE 5; ETHYLHEXYL PALMITATE; ALKYL (C12-15) BENZOATE; PROPANEDIOL; POLYSORBATE 80; GLYCERYL MONOSTEARATE; PEG-100 STEARATE; CETYL ALCOHOL; POLYGLYCERYL-6 ISOSTEARATE; DIMETHICONE; ECHINACEA PURPUREA ROOT; ARONIA MELANOCARPA FRUIT JUICE; TAGETES ERECTA FLOWER; SUNFLOWER OIL; SAFFLOWER OIL; MALIC ACID; TOCOPHEROL; MYRISTIC ACID; GLYCERIN; HYDROGENATED SOYBEAN LECITHIN; PANTHENOL; STEARIC ACID; MICROCRYSTALLINE CELLULOSE; ALUMINUM OXIDE; BEHENIC ACID; STEARYL ALCOHOL; CAPRYLYL TRISILOXANE; CYCLOMETHICONE 6; ISOHEXADECANE; LAURYL PEG-9 POLYDIMETHYLSILOXYETHYL DIMETHICONE; 1,2-HEXANEDIOL; DOCOSANOL; TRIETHOXYCAPRYLYLSILANE; POLYHYDROXYSTEARIC ACID (2300 MW); SODIUM ACRYLATE/SODIUM ACRYLOYLDIMETHYLTAURATE COPOLYMER (4000000 MW); CARBOXYMETHYLCELLULOSE SODIUM, UNSPECIFIED; SORBITAN MONOOLEATE; BUTYLENE GLYCOL; PHENOXYETHANOL; CAPRYLYL GLYCOL; ETHYLHEXYLGLYCERIN; SODIUM BENZOATE; POTASSIUM SORBATE; SODIUM CITRATE; CITRIC ACID MONOHYDRATE; HEXASODIUM PHYTATE

Green Defense Broad Spectrum SPF 30

ACTIVE INGREDIENTS

Titanium Dioxide 2.40%

Zinc Oxide 5.82%

Purpose

Sunscreen

Uses

- helps prevent sunburn
- if used as directed with other sun protection measures (see), decreases the risk of skin cancer and early skin aging caused by the sun. Directions

Warnings

For external use only.

Do not use

on damaged or broken skin.

When using this product

keep out of eyes. Rinse with water to remove.

Stop use and ask a doctor

if rash occurs.

Keep out of reach of children.

If swallowed, get medical help or contact a Poison Control Center right away.

Directions

- Apply liberally 15 minutes before sun exposure
- Use a water resistant sunscreen if swimming or sweating
- Reapply at least every 2 hours
- Spending time in the sun increase your risk of skin cancer and early skin aging. To decrease risk, regularly use a sunscreen with a Broad Spectrum SPF value of 15 or higher and other sun protection measures including: Sun Protection Measure.
- Limit time in the sun, especially from 10 a.m.-2-p.m.
- Wear long sleeved shirts, pants, hats and sunglasses
- Children under 6 months: Ask a doctor

Other information

- Protect the product in this container from excessive heat and direct sunlight.
- You may report a serious adverse event from use of this product to: 1-844-432-7622 Farmacy Beauty LLC. 1111 MacArthur Blvd. Mahwah NJ 07430

Inactive ingredients

Water (Aqua), Ethyl Macadamiate, Cyclopentasiloxane, Ethylhexyl Palmitate, C12-15 Alkyl Benzoate, Propanediol, Polysorbate 80, Glyceryl Stearate, PEG-100 Stearate, Cetyl Alcohol, Polyglyceryl-6 Isostearate, Dimethicone, Echinacea Purpurea Root Extract, Aronia Melanocarpa Fruit Extract, Hydrolyzed Verbascum Thapsus Flower, Tagetes Erecta Flower Extract, Alteromonas Ferment Extract, Helianthus Annuus (Sunflower) Seed Oil, Carthamus Tinctorius (Safflower) Seed Oil, Malic Acid, Tocopherol, Myristic Acid, Glycerin, Hydrogenated Lecithin, Panthenol, Stearic Acid, Microcrystalline Cellulose, Alumina, Behenic Acid, stearyl Alcohol, Carprylyl Methicone, Cyclohexasiloxane, Isohexadecane, Triethoxysilylethyl Polydimethylsiloxyethyl Hexyl Dimethicone, Lauryl PEG-9 Polydimethylsiloxyethyl Dimethicone, 1,2-Hexanediol, Beheny Alcohol, Triethoxycaprylylsilane, Polyhydroxystearic Acid, Sodium Acrylate/Sodium Acryloyldimethyl Taurate Copolymer, Cellulose Gum, sorbitan Oleate, Butylene Glycol, Phenoxyethanol, Caprylyl Glycol, Ethylhexylglycerin, Sodium Benzoate, Potassium Sorbate, Sodium Citrate, Citric Acid, Sodium Phytate